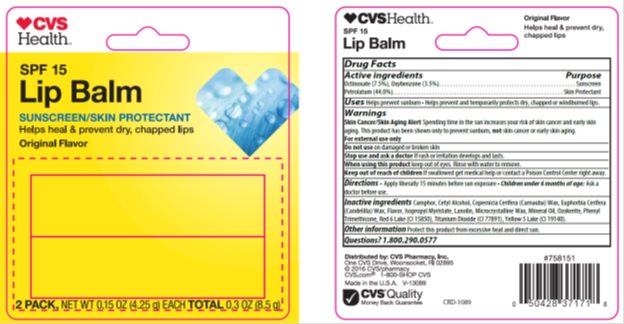 DRUG LABEL: CVS Health Original SPF 15 Lip Balm
NDC: 69842-552 | Form: STICK
Manufacturer: CVS
Category: otc | Type: HUMAN OTC DRUG LABEL
Date: 20160914

ACTIVE INGREDIENTS: OCTINOXATE 7.5 mg/1 g; OXYBENZONE 3.5 mg/1 g; PETROLATUM 44.0 mg/1 g
INACTIVE INGREDIENTS: LIGHT MINERAL OIL 18.00 mg/1 g; MICROCRYSTALLINE WAX 3.00 mg/1 g; LANOLIN 1 mg/1 g; CERESIN 17.3 mg/1 g; ISOPROPYL MYRISTATE .900 mg/1 g

Drug Facts

Active ingredient

Octinoxate (7.5%), Oxybenzone (3.5%)

Petrolatum (44.0%)

Purpose

Sunscreen, Sunscreen, Skin Protectant

Keep Out of Reach of Children

If swallowed get medical help or contact a Poison Control Center right away.

Uses

Helps prevent sunburn. Helps prevent and temporarily protects dry, chapped or windburned lips.

Warnings

Skin Cancer/Skin Aging Alert: Spending time in the sun increases your risk of skin cancer and early skin aging. This product has been shown only to prevent sunburn, not skin cancer or early aging.

For external use only: Stop use and ask a doctor: if rash or irritation develops and lasts.

Directions

Apply liberally before sun exposure and as needed. Children under 6 months of age: Ask a doctor before use.

Inactive Ingredients

Camphor, Cetyl Alcohol, Copernicia Cerifera (Carnauba) Wax, Euphorbia Cerifera (Candelilla) Wax, Flavor, Isopropyl Myristate, Lanolin, Microcrystalline Wax, Mineral Oil, Ozokerite, Phenyl Trimethicone, Red 6 Lake (CI 15850), Titanium Dioxide (CI 77891), Yellow 5 Lake (CI 19140)..